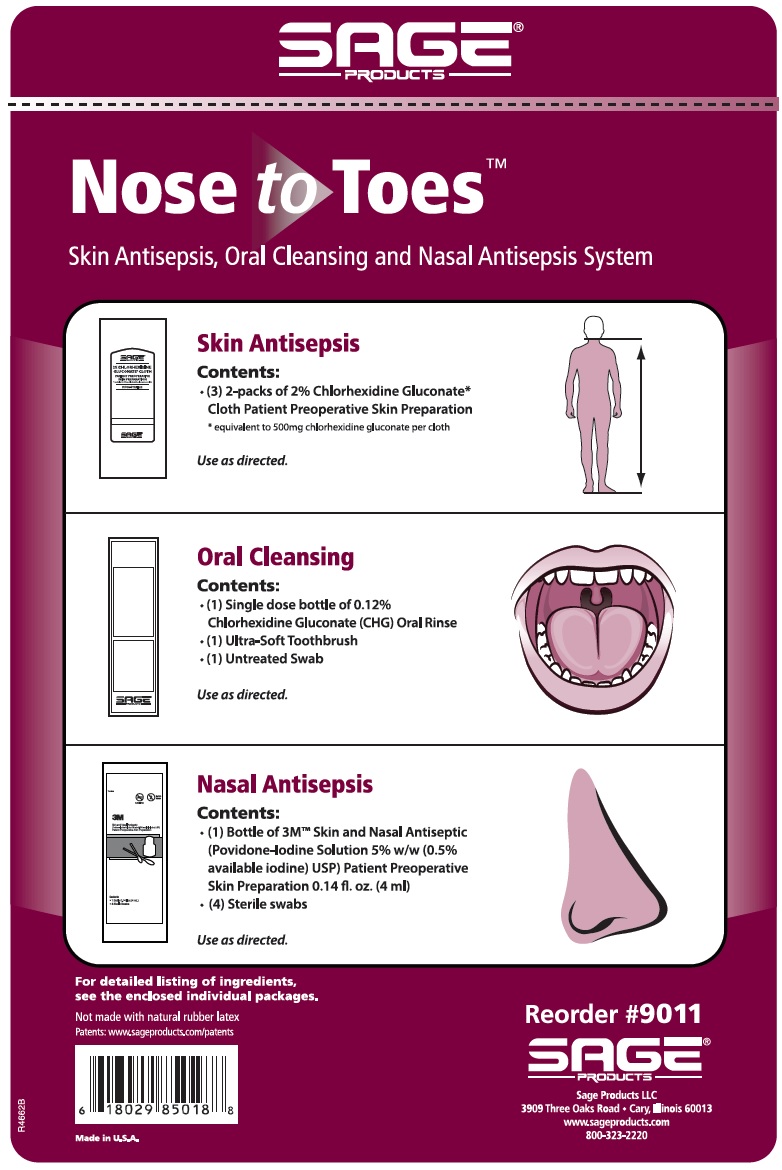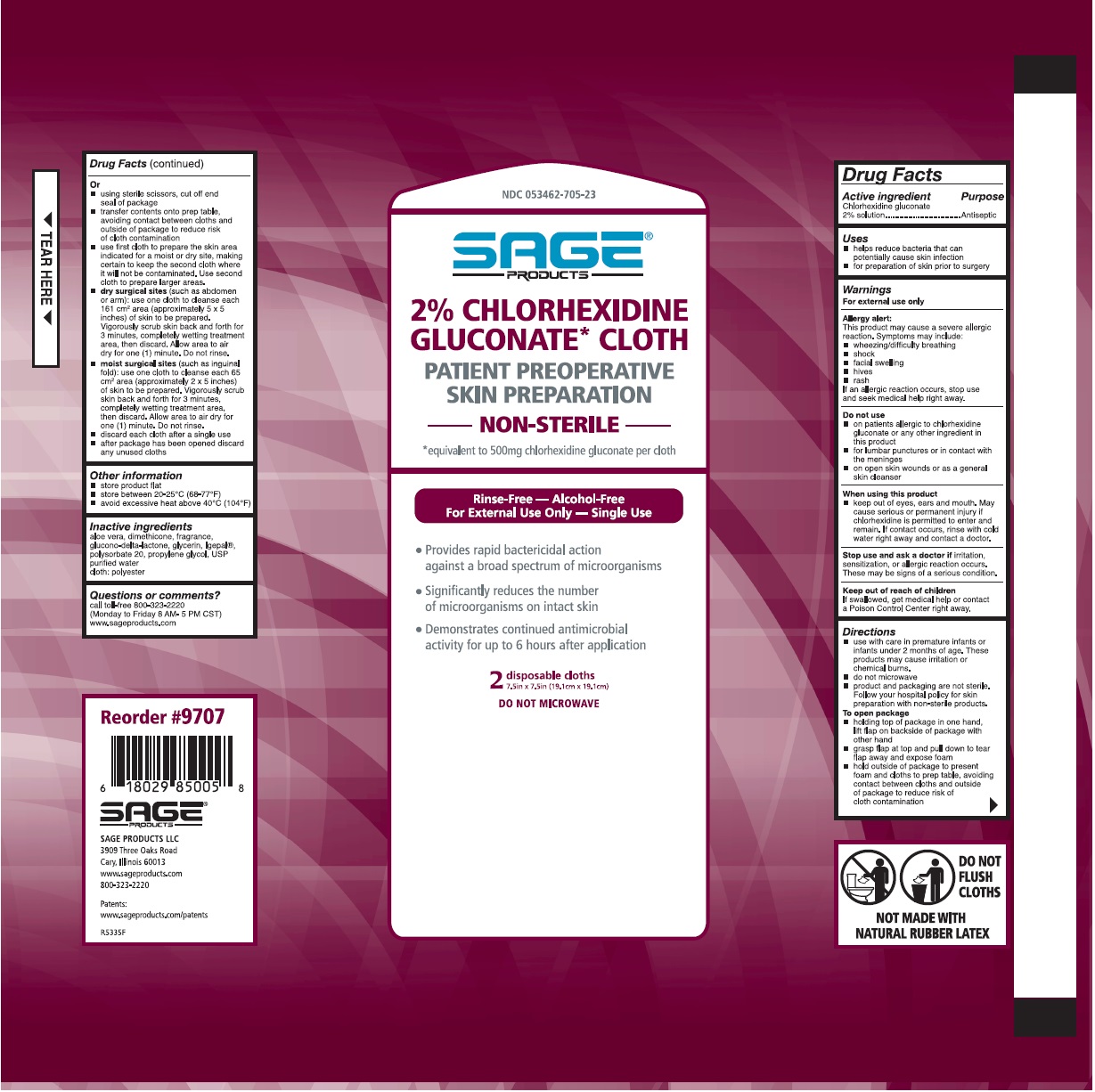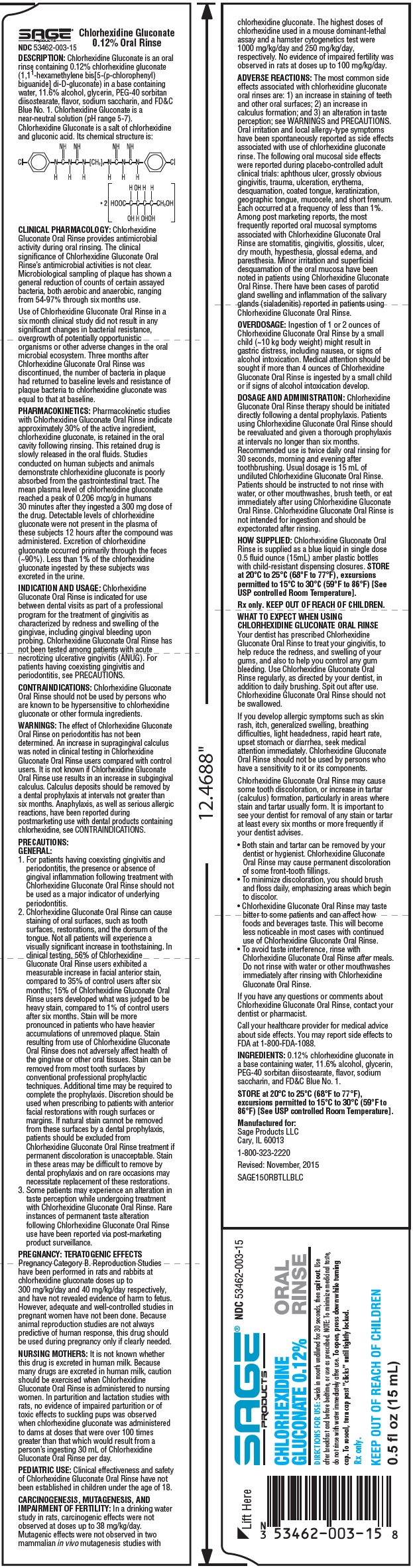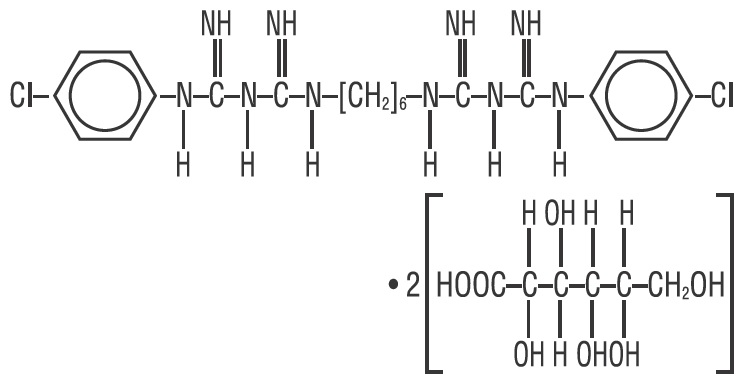 DRUG LABEL: Skin antisepsis, oral cleansing, nasal antisepsis
NDC: 53462-007 | Form: KIT | Route: TOPICAL
Manufacturer: Sage Products LLC
Category: otc | Type: HUMAN OTC DRUG LABEL
Date: 20190529

ACTIVE INGREDIENTS: CHLORHEXIDINE GLUCONATE 500 mg/1 1; POVIDONE-IODINE 5 mg/1 mL; CHLORHEXIDINE GLUCONATE 1.2 mg/1 mL
INACTIVE INGREDIENTS: WATER; NONOXYNOL-9; POLYSORBATE 20; DIMETHICONE 350; PROPYLENE GLYCOL; ALOE VERA LEAF; GLYCERIN; GLUCONOLACTONE; LACTIC ACID; MALIC ACID; SODIUM HYDROXIDE; SODIUM IODIDE; STEARETH-100; WATER; XYLITOL; LAURAMIDOPROPYLAMINE OXIDE; GLYCERIN; PEG-40 SORBITAN DIISOSTEARATE; ALCOHOL; FD&C BLUE NO. 1; WATER; SACCHARIN SODIUM

Skin Antisepsis, oral cleansing, nasal antisepsis

CHLORHEXIDINE GLUCONTATE 0.12% ORAL RINSE DESCRIPTION

Chlorhexidine Gluconate is an oral rinse containing 0.12% chlorhexidine gluconate (1,11-hexamethylene bis[5-(p-chlorophenyl) biguanide] di-D-gluconate) in a base containing water, 11.6% alcohol, glycerin, PEG-40 sorbitan diisostearate, flavor, sodium saccharin, and FD&C Blue No. 1. Chlorhexidine Gluconate is a near-neutral solution (pH range 5-7). Chlorhexidine Gluconate is a salt of chlorhexidine and gluconic acid. Its chemical structure is:

CLINICAL PHARMACOLOGY

Chlorhexidine Gluconate Oral Rinse provides antimicrobial activity during oral rinsing. The clinical significance of Chlorhexidine Gluconate Oral Rinse’s antimicrobial activities is not clear. Microbiological sampling of plaque has shown a general reduction of counts of certain assayed bacteria, both aerobic and anaerobic, ranging from 54-97% through six months use.

Use of Chlorhexidine Gluconate Oral Rinse in a six month clinical study did not result in any significant changes in bacterial resistance, overgrowth of potentially opportunistic organisms or other adverse changes in the oral microbial ecosystem. Three months after Chlorhexidine Gluconate Oral Rinse was discontinued, the number of bacteria in plaque had returned to baseline levels and resistance of plaque bacteria to chlorhexidine gluconate was equal to that at baseline.

PHARMACOKINETICS

Pharmacokinetic studies with Chlorhexidine Gluconate Oral Rinse indicate approximately 30% of the active ingredient, chlorhexidine gluconate, is retained in the oral cavity following rinsing. This retained drug is slowly released in the oral fluids. Studies conducted on human subjects and animals demonstrate chlorhexidine gluconate is poorly absorbed from the gastrointestinal tract. The mean plasma level of chlorhexidine gluconate reached a peak of 0.206 mcg/g in humans 30 minutes after they ingested a 300 mg dose of the drug. Detectable levels of chlorhexidine gluconate were not present in the plasma of these subjects 12 hours after the compound was administered. Excretion of chlorhexidine gluconate occurred primarily through the feces (~90%). Less than 1% of the chlorhexidine gluconate ingested by these subjects was excreted in the urine.

INDICATIONS AND USAGE

Chlorhexidine Gluconate Oral Rinse is indicated for use between dental visits as part of a professional program for the treatment of gingivitis as characterized by redness and swelling of the gingivae, including gingival bleeding upon probing. Chlorhexidine Gluconate Oral Rinse has not been tested among patients with acute necrotizing ulcerative gingivitis (ANUG). For patients having coexisting gingivitis and periodontitis, see PRECAUTIONS.

CONTRAINDICATIONS

Chlorhexidine Gluconate Oral Rinse should not be used by persons who are known to be hypersensitive to chlorhexidine gluconate or other formula ingredients.

WARNINGS

The effect of Chlorhexidine Gluconate Oral Rinse on periodontitis has not been determined. An increase in supragingival calculus was noted in clinical testing in Chlorhexidine Gluconate Oral Rinse users compared with control users. It is not known if Chlorhexidine Gluconate Oral Rinse use results in an increase in subgingival calculus. Calculus deposits should be removed by a dental prophylaxis at intervals not greater than six months. Anaphylaxis, as well as serious allergic reactions, have been reported during postmarketing use with dental products containing chlorhexidine, see CONTRAINDICATIONS.

PRECAUTIONS

GENERAL

1. For patients having coexisting gingivitis and periodontitis, the presence or absence of gingival inflammation following treatment with Chlorhexidine Gluconate Oral Rinse should not be used as a major indicator of underlying periodontitis.
2. Chlorhexidine Gluconate Oral Rinse can cause staining of oral surfaces, such as tooth surfaces, restorations, and the dorsum of the tongue. Not all patients will experience a visually significant increase in toothstaining. In clinical testing, 56% of Chlorhexidine Gluconate Oral Rinse users exhibited a measurable increase in facial anterior stain, compared to 35% of control users after six months; 15% of Chlorhexidine Gluconate Oral Rinse users developed what was judged to be heavy stain, compared to 1% of control users after six months. Stain will be more pronounced in patients who have heavier accumulations of unremoved plaque. Stain resulting from use of Chlorhexidine Gluconate Oral Rinse does not adversely affect health of the gingivae or other oral tissues. Stain can be removed from most tooth surfaces by conventional professional prophylactic techniques. Additional time may be required to complete the prophylaxis. Discretion should be used when prescribing to patients with anterior facial restorations with rough surfaces or margins. If natural stain cannot be removed from these surfaces by a dental prophylaxis, patients should be excluded from Chlorhexidine Gluconate Oral Rinse treatment if permanent discoloration is unacceptable. Stain in these areas may be difficult to remove by dental prophylaxis and on rare occasions may necessitate replacement of these restorations.
3. Some patients may experience an alteration in taste perception while undergoing treatment with Chlorhexidine Gluconate Oral Rinse. Rare instances of permanent taste alteration following Chlorhexidine Gluconate Oral Rinse use have been reported via post-marketing product surveillance.

ADVERSE REACTIONS

The most common side effects associated with chlorhexidine gluconate oral rinses are: 1) an increase in staining of teeth and other oral surfaces; 2) an increase in calculus formation; and 3) an alteration in taste perception; see WARNINGS and PRECAUTIONS. Oral irritation and local allergy-type symptoms have been spontaneously reported as side effects associated with use of chlorhexidine gluconate rinse. The following oral mucosal side effects were reported during placebo-controlled adult clinical trials: aphthous ulcer, grossly obvious gingivitis, trauma, ulceration, erythema, desquamation, coated tongue, keratinization, geographic tongue, mucocele, and short frenum. Each occurred at a frequency of less than 1%. Among post marketing reports, the most frequently reported oral mucosal symptoms associated with Chlorhexidine Gluconate Oral Rinse are stomatitis, gingivitis, glossitis, ulcer, dry mouth, hypesthesia, glossal edema, and paresthesia. Minor irritation and superficial desquamation of the oral mucosa have been noted in patients using Chlorhexidine Gluconate Oral Rinse. There have been cases of parotid gland swelling and inflammation of the salivary glands (sialadenitis) reported in patients using Chlorhexidine Gluconate Oral Rinse.

OVERDOSAGE

Ingestion of 1 or 2 ounces of Chlorhexidine Gluconate Oral Rinse by a small child (~10 kg body weight) might result in gastric distress, including nausea, or signs of alcohol intoxication. Medical attention should be sought if more than 4 ounces of Chlorhexidine Gluconate Oral Rinse is ingested by a small child or if signs of alcohol intoxication develop.

DOSAGE AND ADMINISTRATION

Chlorhexidine Gluconate Oral Rinse therapy should be initiated directly following a dental prophylaxis. Patients using Chlorhexidine Gluconate Oral Rinse should be reevaluated and given a thorough prophylaxis at intervals no longer than six months. Recommended use is twice daily oral rinsing for 30 seconds, morning and evening after toothbrushing. Usual dosage is 15 mL of undiluted Chlorhexidine Gluconate Oral Rinse. Patients should be instructed to not rinse with water, or other mouthwashes, brush teeth, or eat immediately after using Chlorhexidine Gluconate Oral Rinse. Chlorhexidine Gluconate Oral Rinse is not intended for ingestion and should be expectorated after rinsing.

HOW SUPPLIED

Chlorhexidine Gluconate Oral Rinse is supplied as a blue liquid in single dose 0.5 fluid ounce (15mL) amber plastic bottles with child-resistant dispensing closures. STORE at 20°C to 25°C (68°F to 77°F), excursions permitted to 15°C to 30°C (59°F to 86°F) [See USP controlled room temperature].

PATIENT INFORMATION

Rx only. KEEP OUT OF REACH OF CHILDREN.

WHAT TO EXPECT WHEN USING CHLORHEXIDINE GLUCONATE ORAL RINSE
Your dentist has prescribed Chlorhexidine Gluconate Oral Rinse to treat your gingivitis, to help reduce the redness, and swelling of your gums, and also to help you control any gum bleeding. Use Chlorhexidine Gluconate Oral Rinse regularly, as directed by your dentist, in addition to daily brushing. Spit out after use. Chlorhexidine Gluconate Oral Rinse should not be swallowed.

If you develop allergic symptoms such as skin rash, itch, generalized swelling, breathing difficulties, light headedness, rapid heart rate, upset stomach or diarrhea, seek medical attention immediately. Chlorhexidine Gluconate Oral Rinse should not be used by persons who have a sensitivity to it or its components.

Chlorhexidine Gluconate Oral Rinse may cause some tooth discoloration, or increase in tartar (calculus) formation, particularly in areas where stain and tartar usually form. It is important to see your dentist for removal of any stain or tartar at least every six months or more frequently if your dentist advises.

Both stain and tartar can be removed by your dentist or hygienist. Chlorhexidine Gluconate Oral Rinse may cause permanent discoloration of some front-tooth fillings.
To minimize discoloration, you should brush and floss daily, emphasizing areas which begin to discolor.
Chlorhexidine Gluconate Oral Rinse may taste bitter to some patients and can affect how foods and beverages taste. This will become less noticeable in most cases with continued use of Chlorhexidine Gluconate Oral Rinse.
To avoid taste interference, rinse with Chlorhexidine Gluconate Oral Rinse after meals. Do not rinse with water or other mouthwashes immediately after rinsing with Chlorhexidine Gluconate Oral Rinse.
If you have any questions or comments about Chlorhexidine Gluconate Oral Rinse, contact your dentist or pharmacist.

Call your healthcare provider for medical advice about side effects. You may report side effects to FDA at 1-800-FDA-1088.

INGREDIENTS: 0.12% chlorhexidine gluconate in a base containing water, 11.6% alcohol, glycerin, PEG-40 sorbitan diisostearate, flavor, sodium saccharin, and FD&C Blue No. 1.

STORE at 20°C to 25°C (68°F to 77°F), excursions permitted to 15°C to 30°C (59°F to 86°F) [See USP controlled room temperature].

Manufactured for:
Sage Products LLC
Cary, IL 60013

1-800-323-2220

Revised: October, 2018

SAGE15ORBTLLBLB

2% CHLORHEXIDINE GLUCONATE CLOTH

Active Ingredient | Purpose
Chlorhexidine Gluconate 2% Solution | Antiseptic

USES

- helps reduce bacteria that can potentially cause skin infection
- for preparation of skin prior to surgery

WARNINGS

For external use only

Allergy alert:

This product may cause a severe allergic reaction. Symptoms may include:

- wheezing/difficulty breathing
- shock
- facial swelling
- hives
- rash

If an allergic reaction occurs, stop use and seek medical help right away.

Do not use

- on patients allergic to chlorhexidine gluconate or any other ingredient in this product
- for lumbar punctures or in contact with the meninges
- on open skin wounds or as a general skin cleanse

When using this product

- keep out of eyes, ears and mouth. May cause serious or permanent injury if chlorhexidine is permitted to enter and remain. If contact occurs, rinse with cold water right away and contact a doctor.

Stop use and ask a doctor if irritation, sensitization or allergic reaction occurs. These may be signs of a serious condition.

Keep out of reach of children

If swallowed, get medical help or contact a Poison Control Center right away.

KEEP OUT OF REACH OF CHILDREN

If swallowed, get medical help or contact a Poison Control Center right away.

DIRECTIONS

- use with care in premature infants or infants under 2 months of age. These products may cause irritation or chemical burns.
- do not microwave
- product and packaging are not sterile. Follow your hospital policy for skin preparation with non-sterile products.

To open package

- holding top of package in one hand, lift flap on backside of package with other hand
- grasp flap at top and pull down to tear flap away and expose foam
- hold outside of package to present foam and cloths to prep table, avoiding contact between cloths and outside of package to reduce risk of cloth contamination

Or

- using sterile scissors, cut off end seal of package
- transfer contents onto prep table, avoiding contact between cloths and outside of package to reduce risk of cloth contamination
- use first cloth to prepare the skin area indicated for a moist or dry site, making certain to keep the second cloth where it will not be contaminated. Use second cloth to prepare larger areas.
- dry surgical sites (such as abdomen or arm): use one cloth to cleanse each 161 cm2 area (approximately 5 x 5 inches) of skin to be prepared. Vigorously scrub skin back and forth for 3 minutes, completely wetting treatment area, then discard. Allow area to air dry for one (1) minute. Do not rinse.
- moist surgical sites (such as inguinal fold): use one cloth to cleanse each 65 cm2 area (approximately 2 x 5 inches) of skin to be prepared. Vigorously scrub skin back and forth for 3 minutes, completely wetting treatment area, then discard. Allow area to air dry for one (1) minute. Do not rinse.
- discard each cloth after a single use
- after package has been opened discard any unused cloths

Other information

- store product flat
- store between 20-25°C (68-77°F)
- avoid excessive heat above 40°C (104°F)

INACTIVE INGREDIENT

aloe vera, dimethicone, fragrance, glucono-delta-lactone, glycerin, Igepal®, polysorbate 20, propylene glycol, USP purified water

cloth: polyester

QUESTIONS OR COMMENTS?

call toll-free 800-323-2220

(Monday to Friday 8 AM - 5 PM CST)

www.sageproducts.com